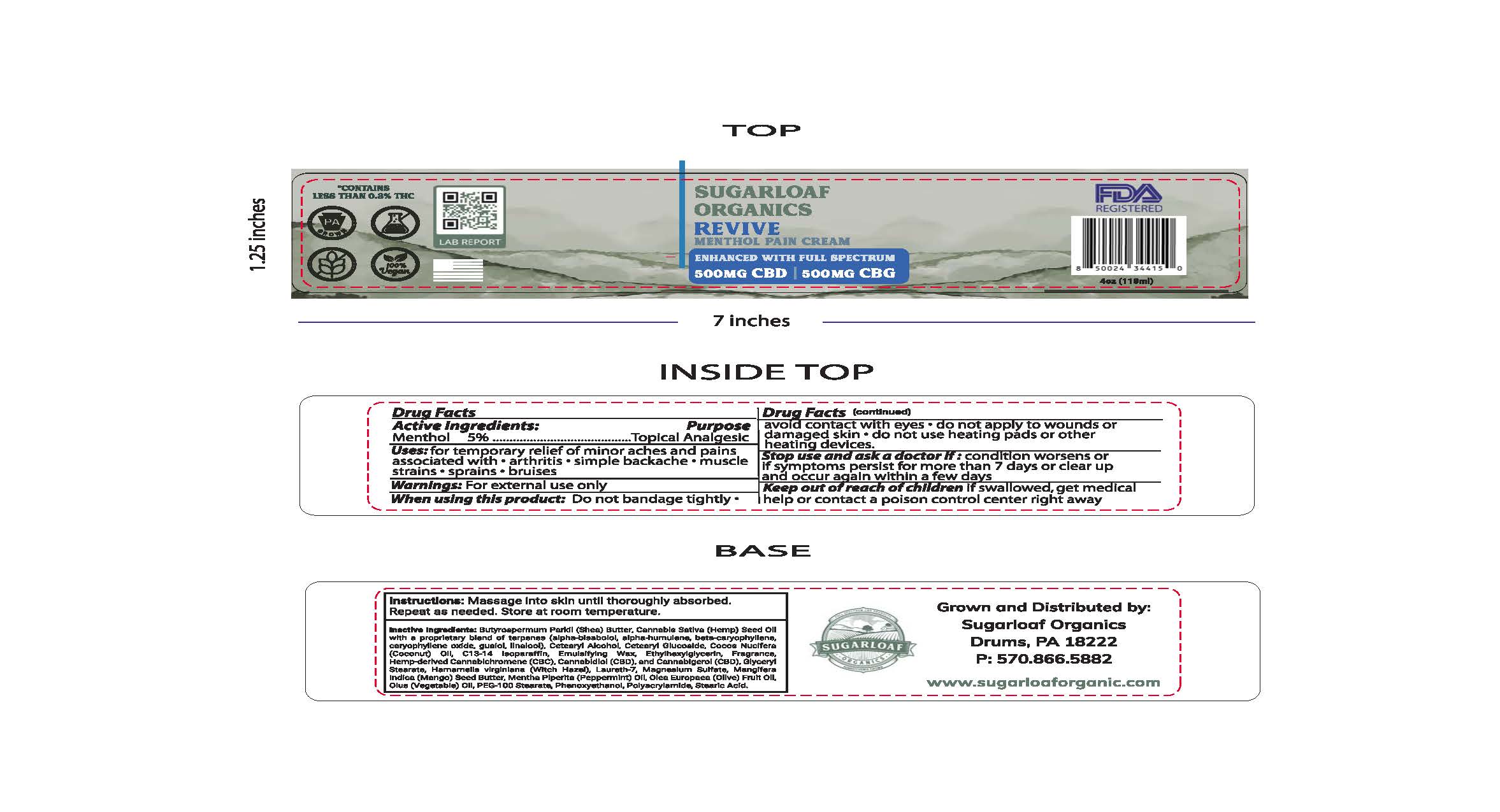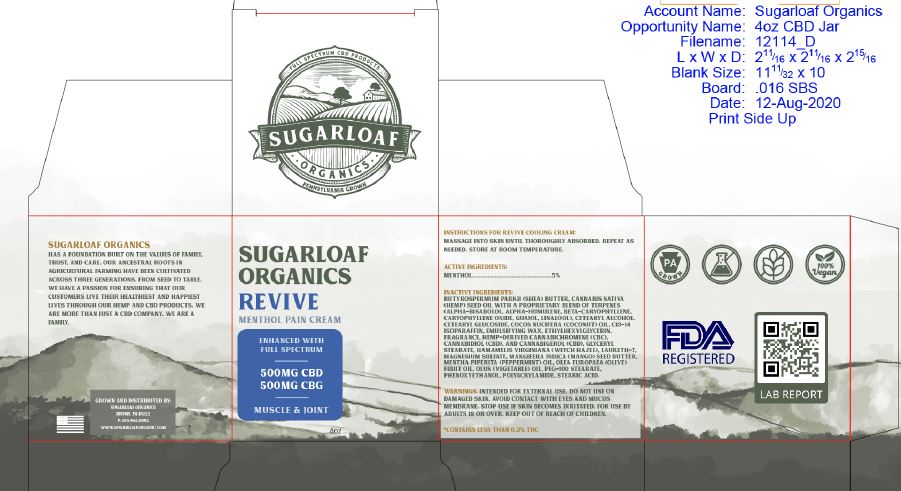 DRUG LABEL: SUGARLOAF ORGANICS MENTHOL REVIVE
NDC: 76348-996 | Form: CREAM
Manufacturer: RENU LABORATORIES, LLC
Category: otc | Type: HUMAN OTC DRUG LABEL
Date: 20250821

ACTIVE INGREDIENTS: MENTHOL 5.9 g/118 mL
INACTIVE INGREDIENTS: CANNABIGEROL; CANNABICHROMENE; PEG-100 STEARATE; WATER; GLYCERYL MONOSTEARATE; OLIVE OIL; WITCH HAZEL; SHEA BUTTER; LAURETH-7; PEPPERMINT OIL; C13-14 ISOPARAFFIN; WHITE WAX; STEARIC ACID; COCONUT OIL; MANGIFERA INDICA SEED BUTTER; CANNABIS SATIVA SEED OIL; CORN OIL; CANNABIDIOL; CETEARYL GLUCOSIDE; PHENOXYETHANOL; MAGNESIUM SULFATE, UNSPECIFIED; POLYACRYLAMIDE (10000 MW); CETOSTEARYL ALCOHOL; ETHYLHEXYLGLYCERIN

SUGARLOAF MENTHOL REVIVE MENTHOL PAIN CREAM

ACTIVE INGREDIENT

Menthol 5%

PURPOSE

Topical Analgesic

INDICATIONS AND USAGE

For temporary relief of minor aches and pains associated with

- arthritis
- simple backache
- muscle strains
- sprains
- bruises

WARNINGS

For external use only

WHEN USING

Do not bandage tightly

- avoid contact with eyes
- do not apply to wounds or damaged skin
- do not use with heating pads or other heating devices.

Stop use and ask a doctor if

- Condition worsens or if symptoms persist for more than 7 days or clear up and occur again within a few days

Keep out of reach of children.

If swallowed, get medical help or contact a Poison Control Center right away.

DOSAGE AND ADMINISTRATION

Instructions: Massage into skin until thoroughtly absorbed. Repeat as needed. Store at room temperature.

INACTIVE INGREDIENT

Butyrospermum Parkii (Shea) Butter, Cannabis Sativa (Hemp) Seed Oil, with a proprietary blend of terpenes (alpha-bisabolol,

alpha-humulene, beta-caryophyllene, caryophyllene oxide, gualol, linalool),

Cetearyl Alcohol, Cetearyl Glucoside, Cocos Nucifera (Coconut) Oil, C13-14 Isoparaffin, Deionized Water, Emulsifying Wax, Ethylhexylglycerin, Fragrance, Hemp-derived Cannabichromene (CBC), Cannabidiol (CBD), and Cannabigerol (CBG),

Glyceryl Stearate, Hamamelis Virginiana (Witch Hazel), Laureth-7, Magnesium Sulfate, Mangifera Indica (Mango) Seed Buter,

Mentha Piperita (Peppermint) Oil, Olea Europaea (Olive) Oil, Olus Oil (Vegetable), PEG-100 Stearate, Phenoxyethanol, Polyacrylamide, Stearic Acid

RECENT MAJOR CHANGES

Indications and Usage This is a clone of another product. Only slight changes to wording have happened. Nothing major.

Dosage and Administration - Directions were simplified.

QUESTIONS

Sugarloaf Organics

Drums, PA 18222

P: 570.866.5882

www.sugarloaforganic.com

PACKAGE LABEL

REFERENCES:

Sugarloaf Organics Revive Menthol Pain Cream

Label and Box AUGUST 2025